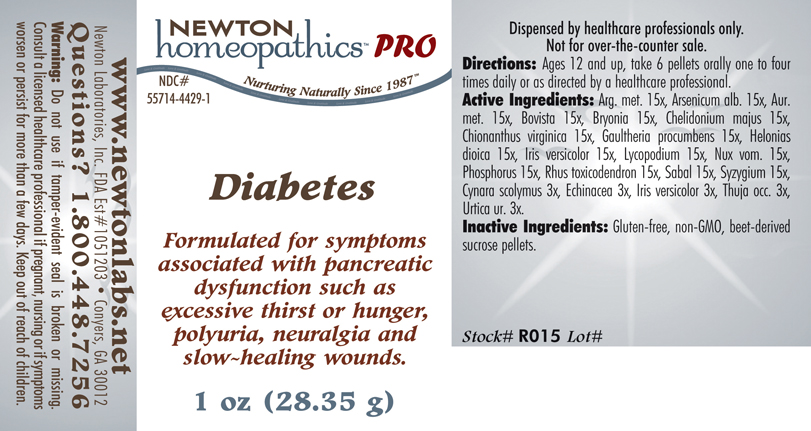 DRUG LABEL: Diabetes 
NDC: 55714-4429 | Form: PELLET
Manufacturer: Newton Laboratories, Inc.
Category: homeopathic | Type: HUMAN PRESCRIPTION DRUG LABEL
Date: 20110601

ACTIVE INGREDIENTS: Silver 15 [hp_X]/1 g; Arsenic Trioxide 15 [hp_X]/1 g; Gold 15 [hp_X]/1 g; Giant Puffball 15 [hp_X]/1 g; Bryonia Alba Root 15 [hp_X]/1 g; Chelidonium Majus 15 [hp_X]/1 g; Chionanthus Virginicus Bark 15 [hp_X]/1 g; Gaultheria Procumbens Top 15 [hp_X]/1 g; Chamaelirium Luteum Root 15 [hp_X]/1 g; Iris Versicolor Root 15 [hp_X]/1 g; Lycopodium Clavatum Spore 15 [hp_X]/1 g; Strychnos Nux-vomica Seed 15 [hp_X]/1 g; Phosphorus 15 [hp_X]/1 g; Toxicodendron Pubescens Leaf 15 [hp_X]/1 g; Saw Palmetto 15 [hp_X]/1 g; Syzygium Cumini Seed 15 [hp_X]/1 g; Cynara Scolymus Leaf 3 [hp_X]/1 g; Echinacea, Unspecified 3 [hp_X]/1 g; Thuja Occidentalis Leafy Twig 3 [hp_X]/1 g; Urtica Urens 3 [hp_X]/1 g
INACTIVE INGREDIENTS: Sucrose

Diabetes

INDICATIONS & USAGE SECTION

Diabetes Formulated for symptoms associated with pancreatic dysfunction such as excessive thirst or hunger, polyuria, neuralgia and slow-healing wounds.

DOSAGE & ADMINISTRATION SECTION

Directions: Ages 12 and up, take 6 pellets orally one to four times daily or as directed by a healthcare professional.

ACTIVE INGREDIENT SECTION

Arg. met. 15x, Arsenicum alb 15x, Aur. met. 15x, Bovista 15x, Bryonia 15x, Chelidonium majus 15x, Chionanthus virginica 15x, Gaultheria procumbens 15x, Helonias dioica 15x, Iris versicolor 15x, Lycopodium 15x, Nux vom 15x, Phosphorus 15x, Rhus toxicodendron 15x, Sabal 15x, Syzygium 15x, Cynara 3x, Echinacea 3x, Iris versicolor 3x, Thuja occ. 3x, Urtica ur. 3x.

PURPOSE SECTION

Formulated for symptoms associated with pancreatic dysfunction such as excessive thirst or hunger, polyuria, neuralgia and slow-healing wounds.

INACTIVE INGREDIENT SECTION

Inactive Ingredients: Gluten-free, non-GMO, beet-derived sucrose pellets.

QUESTIONS? SECTION

www.newtonlabs.net Newton Laboratories, Inc. FDA Est # 1051203 - Conyers, GA 30012
Questions? 1.800.448.7256

WARNINGS SECTION

Warning: Do not use if tamper - evident seal is broken or missing. Consult a licensed healthcare professional if pregnant, nursing or if symptoms worsen or persist for more than a few days. Keep out of reach of children.

PREGNANCY OR BREAST FEEDING SECTION

Consult a licensed healthcare professional if pregnant or nursing or if symptoms worsen or persist for more than a few days.

KEEP OUT OF REACH OF CHILDREN SECTION

Keep out of reach of children.